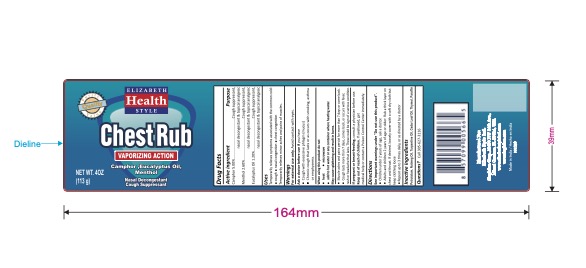 DRUG LABEL: ELIZABETH HEALTH STYLE CHESTRUB VAPORIZING ACTION
NDC: 52920-135 | Form: OINTMENT
Manufacturer: Singhfam Corporation
Category: otc | Type: HUMAN OTC DRUG LABEL
Date: 20241219

ACTIVE INGREDIENTS: CAMPHOR (SYNTHETIC) 5 g/100 g; LEVOMENTHOL 2.6 g/100 g; EUCALYPTUS OIL 1.2 g/100 g
INACTIVE INGREDIENTS: BUTYLATED HYDROXYTOLUENE; CEDAR LEAF OIL; PARAFFIN; LIGHT MINERAL OIL; MICROCRYSTALLINE WAX; NUTMEG OIL; WHITE PINE OIL; THYMOL

Elizabeth Style Chest Rub

Active Ingredient Purpose

Camphor 5.00% ......................... Cough suppressant, nasal decongestant & topical analgesic

Menthol 2.60% .......................... Cough suppressant, nasal decongestant & topical analgesic

Eucalyptus Oil 1.20% .................. Cough suppressant, nasal decongestant & topical analgesic

Use

Temporarily relieves symptoms associated with the common cold:

- cough
- nasal congestion
- chest congestion

Temporarily relieves minor aches and pains of muscles.

Warnings

For external use only. Avoid contact with eyes.
Ask a doctor before use if you have

- Cough with excessive phlegm (mucus)
- Chronic cough that lasts or as occurs with smoking, asthma or emphysema.

When using this product do not

- heat
- microwave
- add to hot water or any container where heating water.

May cause splattering and result in burns.

- Muscle aches and pains persist for more than 7 days or come back.
- Cough lasts more than 7 days, comes back, or occurs with fever, rash or headache that lasts. These could be sign of a serious condition

If pregnant or breast-feeding, consult a physician before use.

Keep out of reach of children. If swallowed, get medical help or contact a Poison Control Center immediately.

Directions

See important warnings under "Do not use this product".

- Children under 2 years of age, ask a doctor.
- Adults and children 2 years of age or older: Rub a thick layer on chest and throat. If desired. loosely cover with a soft dry cloth but keep clothing loose.
- Repeat up to 3 times daily, or as directed by a doctor.

Inactive ingredients

BHT, Cedar Oil, Hard Wax, Light Liquid Paraffin, Micro Wax, Nutmeg Oil, Pine Oil, Thymol.